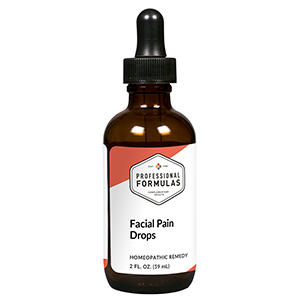 DRUG LABEL: Facial Pain Drops
NDC: 63083-2023 | Form: LIQUID
Manufacturer: Professional Complementary Health Formulas
Category: homeopathic | Type: HUMAN OTC DRUG LABEL
Date: 20190815

ACTIVE INGREDIENTS: SALIX ALBA BARK 3 [hp_X]/59 mL; ACONITUM NAPELLUS WHOLE 4 [hp_X]/59 mL; AMARYLLIS BELLADONNA WHOLE 6 [hp_X]/59 mL; BOS TAURUS NERVE 16 [hp_X]/59 mL
INACTIVE INGREDIENTS: ALCOHOL; WATER

C23

ACTIVE INGREDIENTS

Salix alba 3X
Aconitum napellus 4X
Belladonna 6X
Trigeminal nerve 16X, 30X

QUESTIONS

Professional Formulas

PO Box 2034 Lake Oswego, OR 97035

INDICATIONS

For the temporary relief of mild facial pain, often triggered by chewing, speaking, or brushing teeth.*

PURPOSE

*Claims based on traditional homeopathic practice, not accepted medical evidence. Not FDA evaluated.

WARNINGS

Consult a doctor if condition worsens or if symptoms persist. Keep out of the reach of children. In case of overdose, get medical help or contact a poison control center right away. If pregnant or breastfeeding, ask a healthcare professional before use.

Keep out of the reach of children.

PREGNANCY OR BREAST FEEDING

If pregnant or breastfeeding, ask a healthcare professional before use.

DIRECTIONS

Place drops under tongue 30 minutes before/after meals. Adults and children 12 years and over: Take 10 drops up to 3 times per day for up to 6 weeks. For immediate onset of symptoms, take 10 to 15 drops every 15 minutes up to 3 hours. For less severe symptoms, take 10-15 drops hourly up to 8 hours. Consult a physician for use in children under 12 years of age.

OTHER INFORMATION

Tamper resistant. If seal is broken, do not use. After opening, close container tightly and store at room temperature away from heat.

INACTIVE INGREDIENTS

20% ethanol, purified water.

LABEL

Est 1985

Professional Formulas

Complementary Health

Facial Pain Drops

Homeopathic Remedy

2 FL. OZ. (59 mL)